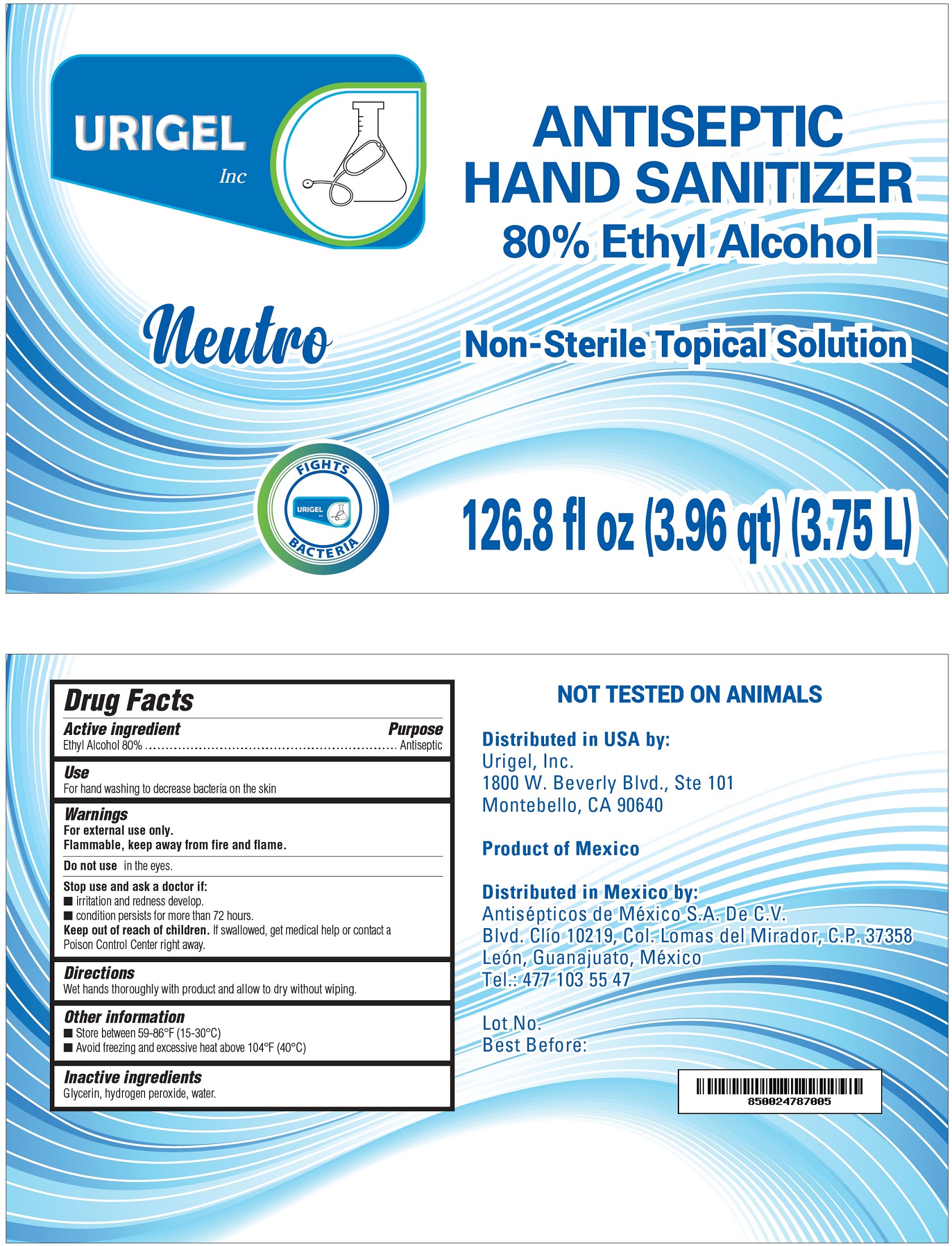 DRUG LABEL: URIGEL Neutro Hand Sanitizer Gel 80%
NDC: 76554-375 | Form: GEL
Manufacturer: Antisépticos de México, S.A. de C.V.
Category: otc | Type: HUMAN OTC DRUG LABEL
Date: 20210111

ACTIVE INGREDIENTS: ALCOHOL 0.8 mL/0.8 mL
INACTIVE INGREDIENTS: GLYCERIN; HYDROGEN PEROXIDE; PARAFFIN; WATER; CARBOMER 940

URIGEL 3.75ML/1GAL 80% ALCOHOL SANITIZER GEL

Active Ingredient(s)

Alcohol 80% v/v. Purpose: Antiseptic

Purpose

Antiseptic, Hand Sanitizer

Use

Hand Sanitizer to help reduce bacteria that potentially can cause disease. For hand washing to decrease bacteria on the skin

Warnings

For external use only. Flammable. Keep away from heat or flame

Do not use

- in children less than 2 months of age
- on open skin wounds

When using this product keep out of eyes, ears, and mouth. In case of contact with eyes, rinse eyes thoroughly with water.
Stop use and ask a doctor if irritation or rash occurs. These may be signs of a serious condition.
Keep out of reach of children. If swallowed, get medical help or contact a Poison Control Center right away.

Stop use and ask a doctor if irritation or rash occurs. These may be signs of a serious condition.

Keep out of reach of children. If swallowed, get medical help or contact a Poison Control Center right away.

Directions

- Wet hands thoroughly with product and allow to dry without wiping

Other information

- Store between 15-30C (59-86F)
- Avoid freezing and excessive heat above 40C (104F)

Inactive ingredients

Glycerin, hydrogen peroxide, water USP. paraffib, carbopol 940

Package Label - Principal Display Panel 3.75ML 80%

3.75ML NDC 76554-375-10